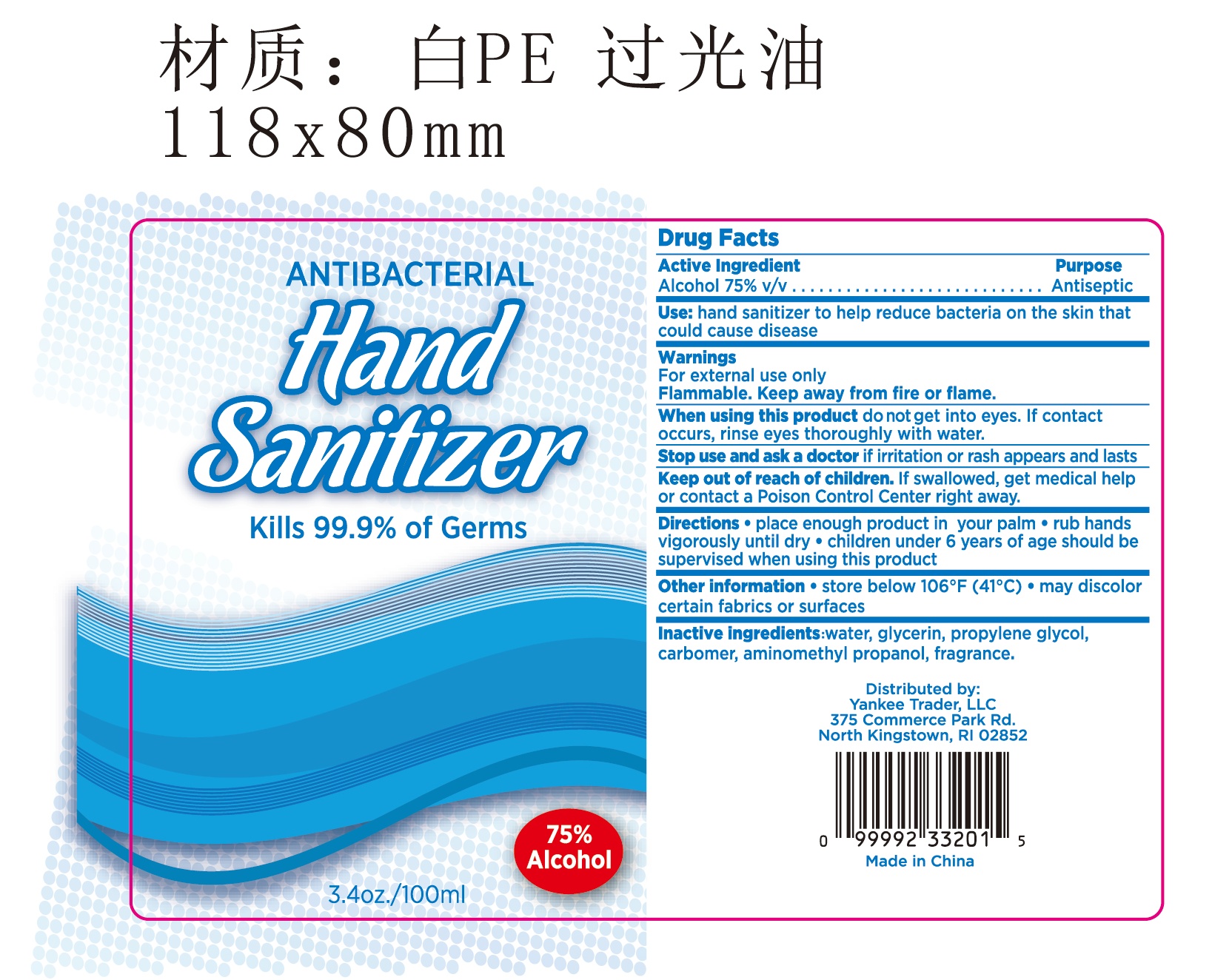 DRUG LABEL: Antibacterial hand sanitizer original 100ml
NDC: 54860-352 | Form: GEL
Manufacturer: Shenzhen Lantern Scicence Co Ltd
Category: otc | Type: HUMAN OTC DRUG LABEL
Date: 20210223

ACTIVE INGREDIENTS: ALCOHOL 75 mL/100 mL
INACTIVE INGREDIENTS: PROPYLENE GLYCOL 0.01 mL/100 mL; LEMON 0.1 mL/100 mL; CARBOMER 940 0.35 mL/100 mL; AMINOMETHYLPROPANOL 0.11 mL/100 mL; WATER 24.42 mL/100 mL; GLYCERIN 0.01 mL/100 mL

Antibacterial hand sanitizer original 100ml

Active Ingredient

Active Ingredient purpose

Alcohol 75% v/v Antiseptic

use

hand sanitizer to help reduce bacteria on the skin that could cause disease.

DOSAGE AND ADMINISTRATION

Recommended for repeated use.

use anywhere without water.

Warning

For external use only

Flammable,keep away from fire or flame.

When using this product,do not get into eyes,If contact occurs,rinse eyes thoroughly with water.

Stop use and ask a doctor, If irritation or rash appears and lasts.

Keep out of reach of children.If swallowed,get medical help or contact a Poison control center right away.

WARNINGS AND PRECAUTIONS

For external use only.

Flammable, keep away from heat and flame.

STOP USE

Discontinue if skin becomes irritated and ask a doctor .

Keep out of reach of children. In case of accidental ingestion, seek professional assistance or contact a poson control center immediately.

Inactive ingredients

Water, Glycerin,Propylene Glycol,Carbomer,,Aminomethyl propanol,fragrance.

Directions

place enough product in your palm. rub hands vigorously until dry.children under 6 years of age should be supervised when using this product.

When using this product

keep out of eyes. In case of contact with eyes, flush thoroughly with water.

Do not inhale or ingest.

Avoid contact with broken skin.

Other information

Do not store above 105F.

May discolor some fabrics.

Harmful to wood finishes and plastics.

other information

store below 106 ℉（41℃),may discolor certain fabrics or surfaces